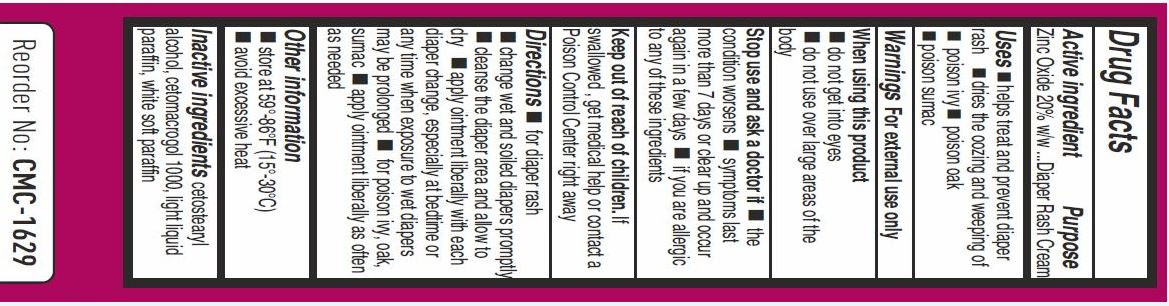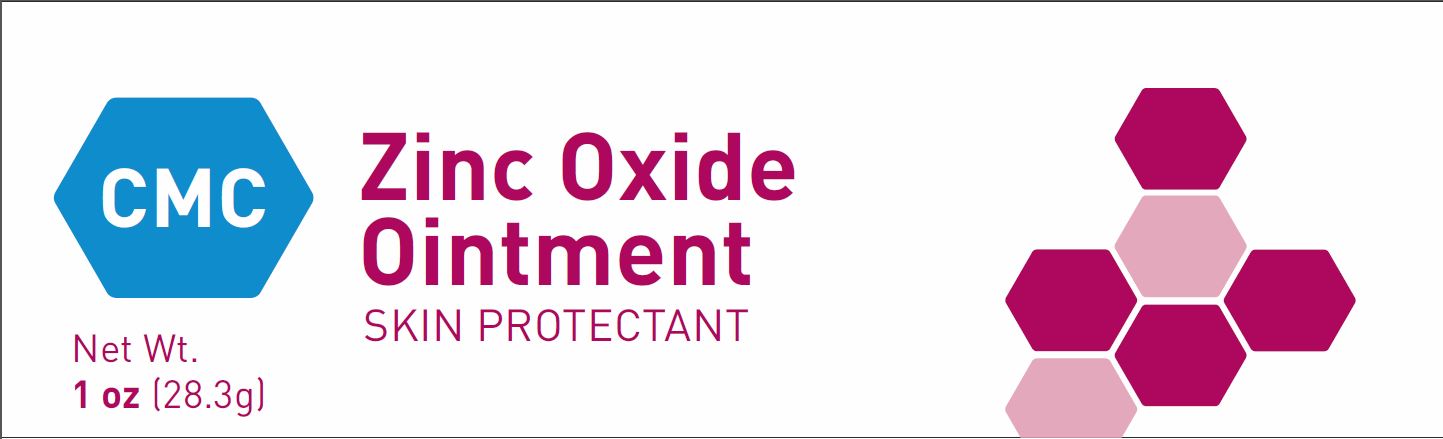 DRUG LABEL: CMC ZINC OXIDE
NDC: 71168-3040 | Form: OINTMENT
Manufacturer: SKYLARK CMC PRIVATE LIMITED
Category: otc | Type: HUMAN OTC DRUG LABEL
Date: 20170911

ACTIVE INGREDIENTS: ZINC OXIDE 20 g/100 g
INACTIVE INGREDIENTS: CETETH-20; PETROLATUM; CETOSTEARYL ALCOHOL; LIGHT MINERAL OIL

SKYLARK ZINC OXIDE 20% DIAPER RASH CREAM

Active ingredient

Zinc Oxide (20% w/w)

Purpose

Skin Protectant

Purpose

- helps treat and prevent diaper rash
- dries the oozing and weeping of poison ivy, poison oak, poison sumac

Warnings

For external use only

When using this product

- do not get into eyes
- do not use over large areas of the body

Stop use and ask a doctor if

- if condition worsens
- symptoms last more than 7 days or clear up and occur again within a few days
- if you are allergic to any of these ingredients

Keep out of reach of children

- if swallowed, get medical help or contact a Poison Control Center right away

Directions

- for diaper rash
- change wet and soiled diapers promptly
- cleanse the diaper area and allow to dry
- apply ointment liberally with each diaper change, especially at bedtime or any time when exposure to wet diapers may be prolonged
- for poison ivy, oak, sumac
- apply ointment liberally as often as needed

Other information

- store at 56°-86° F (15-30°C)
- avoid excessive heat

Inactive ingredients

cetostearyl alcohol, cetomacrogol 1000, light liquid paraffin, white soft paraffin